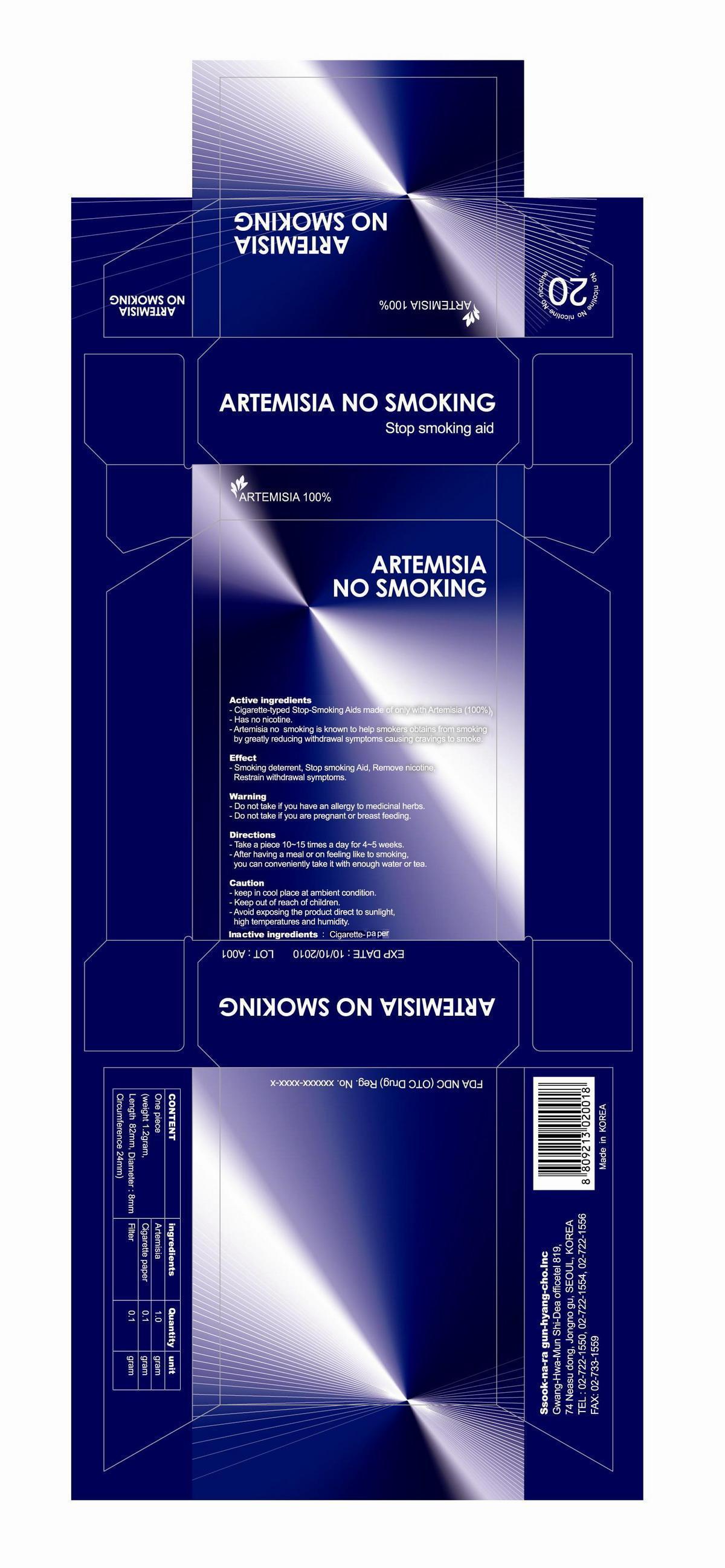 DRUG LABEL: Artemisia No Smoking
NDC: 70378-001 | Form: INHALANT
Manufacturer: KOREA STOP Smoking science CO., LTD.
Category: otc | Type: HUMAN OTC DRUG LABEL
Date: 20160107

ACTIVE INGREDIENTS: WORMWOOD 1 g/1 g
INACTIVE INGREDIENTS: FLATHEAD SOLE; WATER

Drug Facts

ACTIVE INGREDIENT

artemisia

INACTIVE INGREDIENT

flathead sole

PURPOSE

Cigarette-typed Stop-Smoking Aids made of only with Artemisia (100%)
Has no nicotine.
Artemisia no smoking is known to help smokers obtains from smoking by greatly reducing withdrawal symptoms causing cravings to smoke

keep out of reach of the children

INDICATIONS AND USAGE

- Beneficial to health of smokers
- helpful to those who want to stop smoking
- provides effect of artemisia to ordinary prople as a well-being product

WARNINGS

- Do not take if you have an allergy to medicinal herbs.
- Do not take if you are pregnant or breast feeding

DOSAGE AND ADMINISTRATION

for external use only